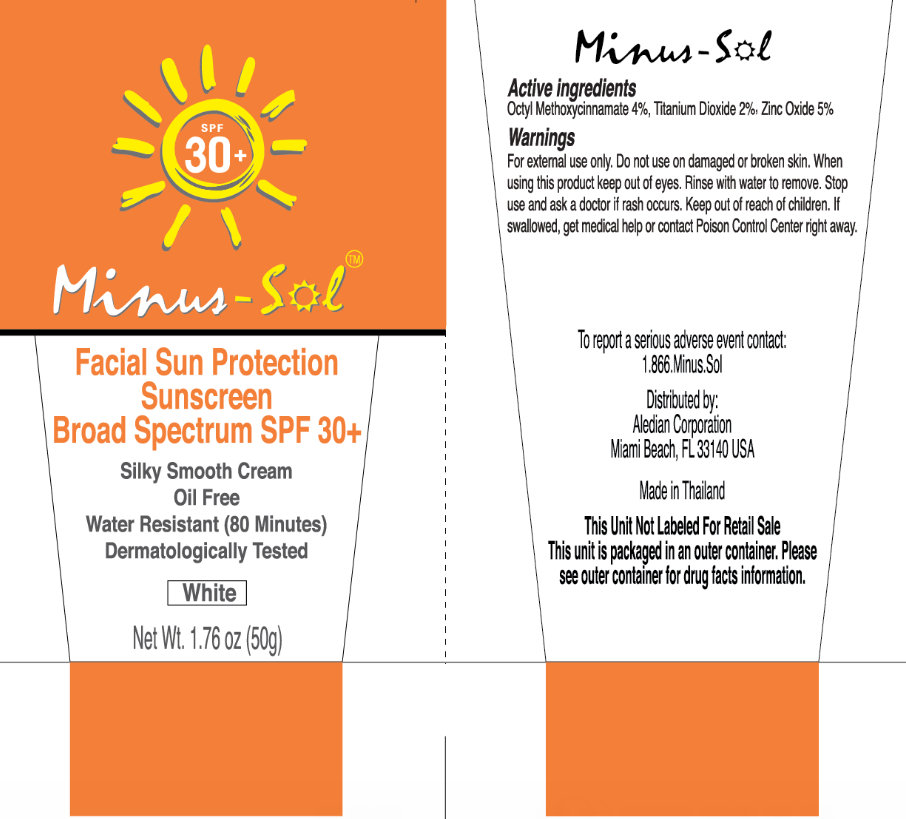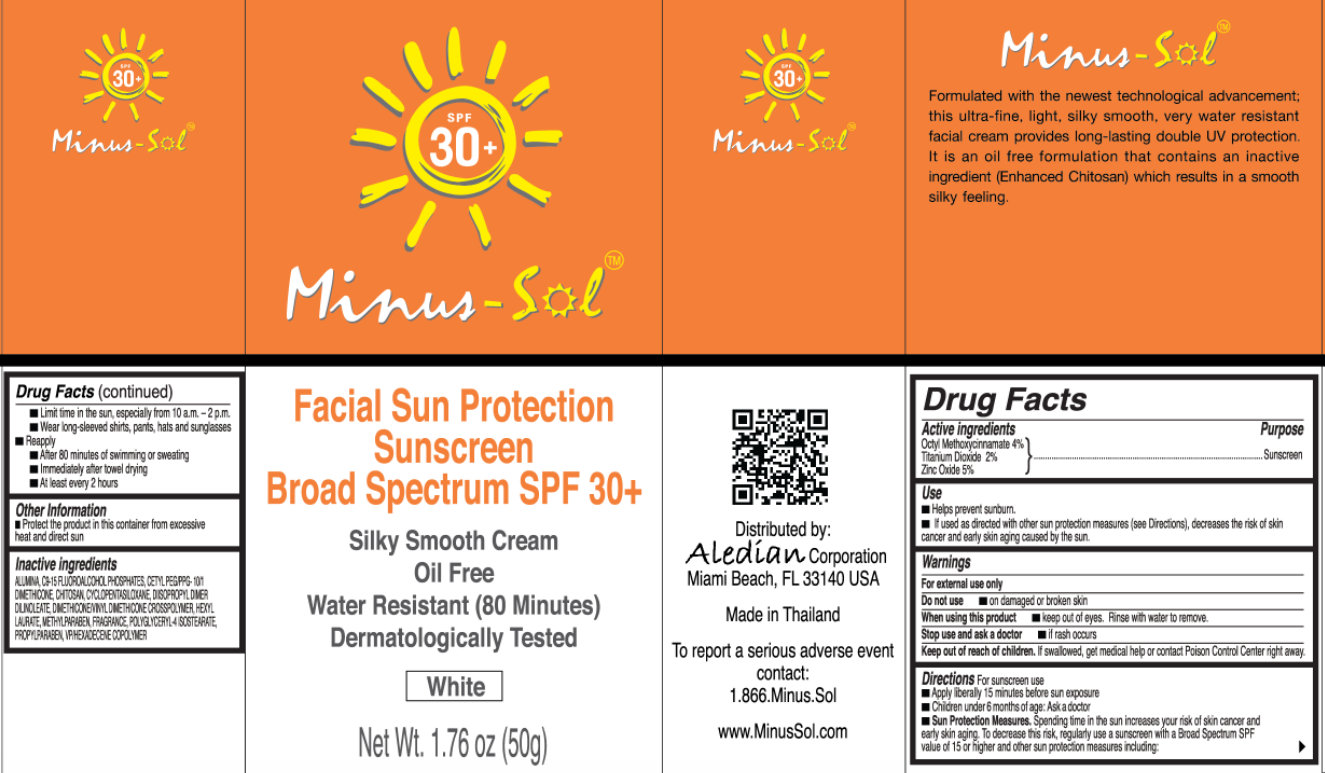 DRUG LABEL: Minus-Sol Facial Sun Protection Sunscreen Broad Spectrum SPF 30 Plus White
NDC: 68411-4057 | Form: CREAM
Manufacturer: Aledian Corporation
Category: otc | Type: HUMAN OTC DRUG LABEL
Date: 20130318

ACTIVE INGREDIENTS: OCTINOXATE 4 g/100 g; TITANIUM DIOXIDE 2 g/100 g; ZINC OXIDE 5 g/100 g
INACTIVE INGREDIENTS: ALUMINUM OXIDE; CYCLOMETHICONE 5; HEXYL LAURATE; FERROSOFERRIC OXIDE; FERRIC OXIDE RED; FERRIC OXIDE YELLOW; METHYLPARABEN; POLYGLYCERYL-4 ISOSTEARATE; PROPYLPARABEN

Minus-Sol Facial Sun Protection Sunscreen Broad Spectrum SPF 30 Plus White

Active ingredients

Octyl Methoxycinnamate 4%
Titanium Dioxide 5%
Zinc Oxide 5%

Purpose

Sunscreen

Use

- Helps prevent sunburn
- If used as directed with other sun protection measures (see Directions), decreases the risk of skin cancer and early skin aging caused by the sun.

Warnings

For external use only

Do not use

- on damaged or broken skin

When using this product

- keep out of eyes. Rinse with water to remove.

Stop use and ask a doctor

- if rash occuurs

Keep out of reach of children.

If swallowed, get medical help or contact Poison Control Center right away.

Directions:

For sunscreen use

- Apply liberally 15 minutes before sun exposure
- Children under 6 months of age: Ask a doctor
- Sun Protection Measures: Spending time in the sun increases your risk of skin cancer and early skin aging. To decrease this risk, regularly use a sunscreen with a Broad Spectrum SPF value of 15 or higher and other sun protection measures including
- Limit time in the sun, especially from 10 a.m. - 2 p.m.
- Wear long-sleeved shirts, pants, hats and sunglasses
- Reapply
- After 80 minutes of swimming or sweating
- Immediately after towel drying
- At least every 2 hours

Other information

- Protect the product in this container from excessive heat and direct sun

Inactive ingredients

ALUMINA, C9-15 FLUCROALCOHOL PHOSPHATES, CETYL PPG/PPG-10/1 DIMETHICONE, CHITOSAN, CYCLOPENTASILOXANE, DISOPROPYLOMER DUNCLEATE, DIMETHOCONEVINYL DIMETHICONE CROSSPOLYMER, HEXYL LAURATE, IRON OXIDE BLACK, IRON OXIDE RED, IRON OXIDE YELLOW METHYLPARABEN, FRAGRANCE, POLYGLYCERY-4 ISOSTEARATE, PROPYLPARABEN, PHEXACECENE COPOLYMER.

Minus-sol

Formulated with the newest technological advancement; this ultra-fine, light, silky smooth, very water resistant facial cream provides long-lasting double UV protection. It is an oil free formulation that contains an inactive ingredient (Enhanced Chitosan) which results in a smooth silky feeling.
Distributed by:
Aledian Corporation
Miami Beach, FL 33140 USA
Made in Thailand
To report a serious adverse event
Contact:
1.866.Minus.Sol
www.MinusSol.com

PACKAGE LABEL

SPF 30+ Minus-Sol
Facial Sun Protection Sunscreen Broad Spectrum SPF 30+
Silky Smooth Cream Oil Free
Water Resistant (80 Minutes)
Dermatologically Tested
White
Net Wt. 1.76 oz (50g)